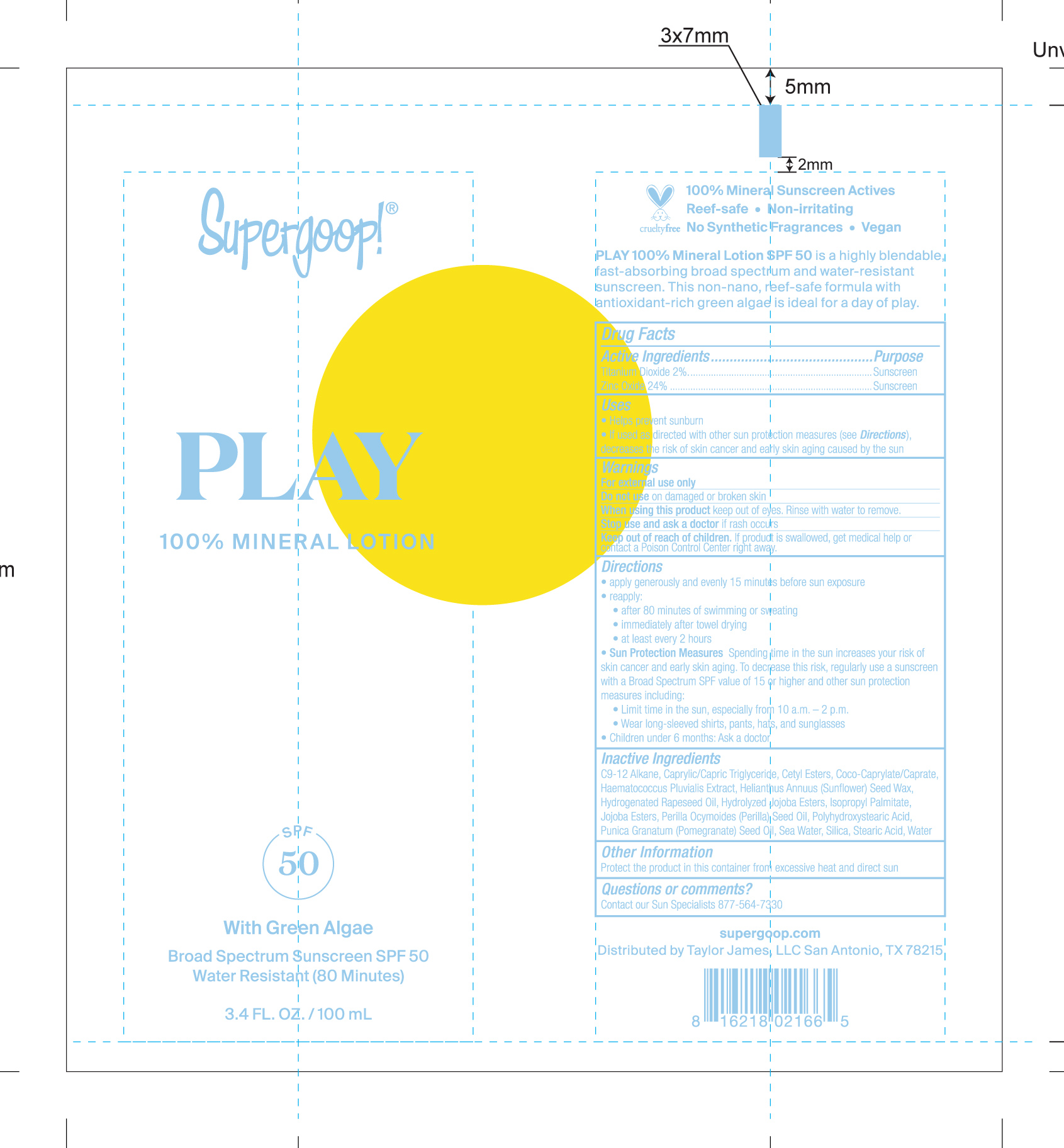 DRUG LABEL: Play Mineral Broad Spectrum SPF 50
NDC: 75936-175 | Form: LOTION
Manufacturer: Supergoop, LLC
Category: otc | Type: HUMAN OTC DRUG LABEL
Date: 20221027

ACTIVE INGREDIENTS: TITANIUM DIOXIDE 2 g/100 mL; ZINC OXIDE 24 g/100 mL
INACTIVE INGREDIENTS: CETYL ESTERS WAX; COCO-CAPRYLATE/CAPRATE; PERILLA FRUTESCENS SEED OIL; SILICON DIOXIDE; HYDROLYZED JOJOBA ESTERS (ACID FORM); HAEMATOCOCCUS PLUVIALIS; HELIANTHUS ANNUUS SEED WAX; HYDROGENATED RAPESEED OIL; ISOPROPYL PALMITATE; POLYHYDROXYSTEARIC ACID (2300 MW); POMEGRANATE SEED OIL; STEARIC ACID; WATER; SODIUM CHLORIDE; MEDIUM-CHAIN TRIGLYCERIDES

Play 100% Mineral Lotion Broad Spectrum Sunscreen SPF 50

Active Ingredients Purpose

Titanium Dioxide 2% Sunscreen

Zinc Oxide 24% Sunscreen

Uses

- Helps Prevent sunburn
- If used as directed with other sun protection measures (see Directions), decreases the risk of skin cancer and early skin aging caused by the sun

Keep out of reach of children. If product is swallowed, get medical help or contact a Poison Control Center right away.

Stop use and ask a doctor if rash occurs.

Warnings

For external use only

Do not use on damaged or broken skin.

When using this product keep out of eyes. Rinse with water to remove.

Directions

Apply liberally 15 minutes before sun exposure
Reapply:

- after 80 minutes of swimming or sweating
- Immediately after towel drying
- At least every 2 hours

Sun Protection Measures. Spending time in the sun increases your risk of skin cancer and early skin aging. To decrease this risk, regularly use a sunscreen with a Broad Spectrum SPF value 15 or higher and other sun protection measures including:

- Limit time in the sun, especially from 10a.m. – 2p.m.
- Wear long-sleeve shirts, pants, hats, and sunglasses
- Children under 6 months: Ask a doctor

Inactive Ingredients

C9-12 Alkane, Caprylic/Capric Triglyceride, Cetyl Esters, Coco-Caprylate/Caprate, Haematococcus Pluvalis Extract, Helianthus Annuus (Sunflower) Seed Wax, Hydrogenated Rapeseed Oil, Hydrogenated Rapeseed Oil, Hydrolyzed Jojoba Esters, Isopropyl Palmitate, Jojoba Esters, Perilla Ocymoides (Perilla) Seed Oil, Polyhydroxystearic Acid, Punica Granatum (Pomegranate) Seed Oil, Sea Water, Silica, Stearic Acid, Water

PACKAGE LABEL

Play 100% Mineral Lotion

with green Algae

Broad Spectrum Sunscreen SPF 50

Water Resistant (80 Minutes)